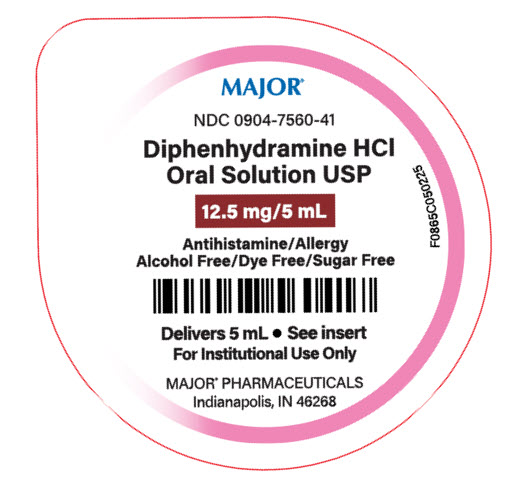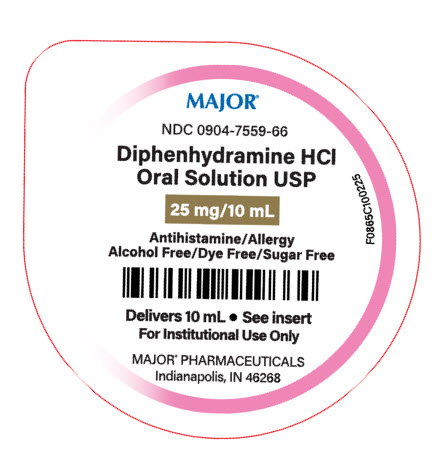 DRUG LABEL: Diphenhydramine HCl
NDC: 0904-7560 | Form: SOLUTION
Manufacturer: Major Pharmaceuticals
Category: otc | Type: HUMAN OTC DRUG LABEL
Date: 20250801

ACTIVE INGREDIENTS: DIPHENHYDRAMINE HYDROCHLORIDE 12.5 mg/5 mL
INACTIVE INGREDIENTS: ANHYDROUS CITRIC ACID; GLYCERIN; WATER; SACCHARIN SODIUM; SODIUM BENZOATE; CARBOXYMETHYLCELLULOSE SODIUM; SODIUM CITRATE, UNSPECIFIED FORM; SORBITOL

Diphenyhydramine HCl Oral Solution, USP

Drug Facts

Active ingredient (in each 5 mL)

Diphenhydramine HCl 12.5 mg

Purpose

Antihistamine

Uses

- temporarily relieves these symptoms due to hay fever or other upper respiratory allergies:
  - runny nose
  - sneezing
  - itchy, watery eyes
  - itching of the nose or throat

Warnings

Do no use

- to make a child sleepy
- with any other product containing diphenhydramine, even one used on skin

Ask a doctor before use if the child has

- a breathing problem such as chronic bronchitis
- glaucoma

When using this product

- marked drowsiness may occur
- sedatives and tranquilizers may increase drowsiness
- excitability may occur, especially in children

Keep out of reach of children.

In case of overdose, get medical help or contact a Poison Control Center right away. (1-800-222-1222)

Directions:

- find right dose on chart below
- mL = milliliter
- take every 4 to 6 hours, or as directed by a doctor
- do not take more than 6 doses in 24 hours

Age (yr) | Dose (mL)
children under 2 years | do not use
children 2 to 5 years | do not use unless directed by a doctor
children 6 to 11 years | 5 mL to 10 mL

Other information

- each 5 mL contains: sodium 10 mg
- store between 20° to 25°C (68° to 77°F).

Diphenhydramine HCl Oral Solution, USP is a clear, cherry flavored liquid supplied in the following:

NDC 0904-7560-41: 5 mL unit dose cup, in a tray of 10 cups.
NDC 0904-7559-66: 10 mL unit dose cup, in a tray of 10 cups.

Inactive ingredients:

citric acid anhydrous, glycerin, flavoring, purified water, saccharin sodium, sodium benzoate, sodium carboxymethylcellulose, sodium citrate, sorbitol.

Questions or comments?

Call 1-800-845-8210

R02/25

Distributed by:

MAJOR® PHARMACEUTICALS
Indianapolis, IN 46268

PRINCIPAL DISPLAY PANEL

Delivers 5 mL

NDC0904-7560-41

Diphenydramine HCl Oral Solution USP

12.5 mg/5 mL

PRINCIPAL DISPLAY PANEL

Delivers 10 mL

NDC0904-7559-66

Diphenydramine HCl Oral Solution USP

25 mg/10 mL